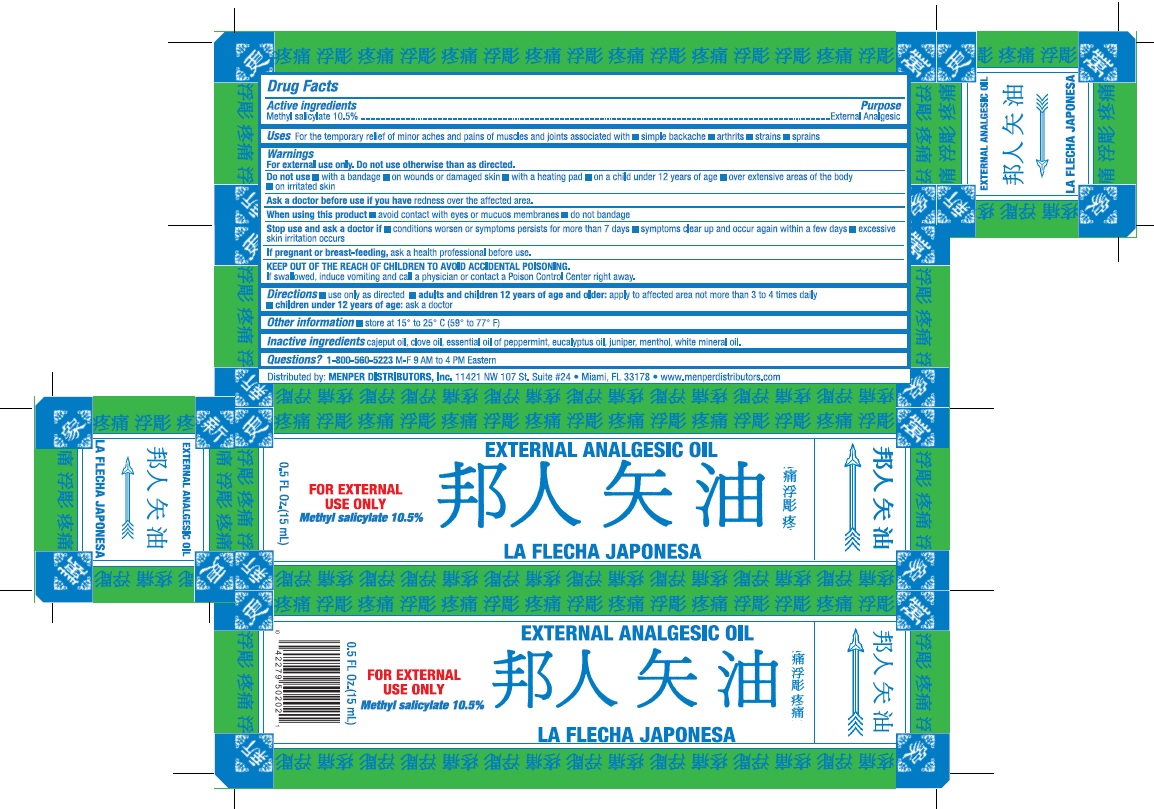 DRUG LABEL: La Flecha Japonesa
NDC: 53145-047 | Form: OIL
Manufacturer: Menper Distributors, Inc.
Category: otc | Type: HUMAN OTC DRUG LABEL
Date: 20250722

ACTIVE INGREDIENTS: METHYL SALICYLATE 105 mg/1 mL
INACTIVE INGREDIENTS: CAJUPUT OIL; CLOVE OIL; PEPPERMINT OIL; EUCALYPTUS OIL; JUNIPER BERRY OIL; MENTHOL; MINERAL OIL

La Flecha Japonesa

Drug Facts

Active Ingredients Purpose

Methyl Salicate 10.5%..............................................................External Analgesic

Purpose

External Analgesic

Uses

For the temporary relief of minor aches and pains of muscles and joints associated with:

- simple backache
- arthrits
- strains
- sprains

WARNINGS

For external use only. Do not use otherwise than as directed.

Do not use

- with a bandage
- on wounds or damage skin
- with a heating pad
- on a child under 12 years of age
- over extensive areas of the body
- on irritated skin

Ask a doctor before use if you have

redness over the affected area

When using this product

- avoid contact with eyes or mucuos membranes
- do not bandage

Stop use and ask a doctor if

- condition worsen or symptoms persists for more than 7 days
- symptoms clear up and occur again within a few days
- excessive skin irritation occurs

if pregnant or breast-feeding

ask a health professional before use

Keep out of the reach of children to avoid accidental poisoning.

If swallowed, induce vomiting and call a physician or contact a Poison Control Center right away.

Directions

use only as directed

- adults and children 12 years of age and older: apply to affected area no more than 3 to 4 times daily
- children under 12 years of age: ask a doctor

Other information

- store at 15° to 25° C (59° to 77° F)

Inactive Ingredients

cajeput oil, clove oil, essential oil of peppermint, eucalyptus oil, juniper, menthol, white mineral oil.

Questions?

1-800-560-5223 M-F 9 AM to 4 PM Eastern.